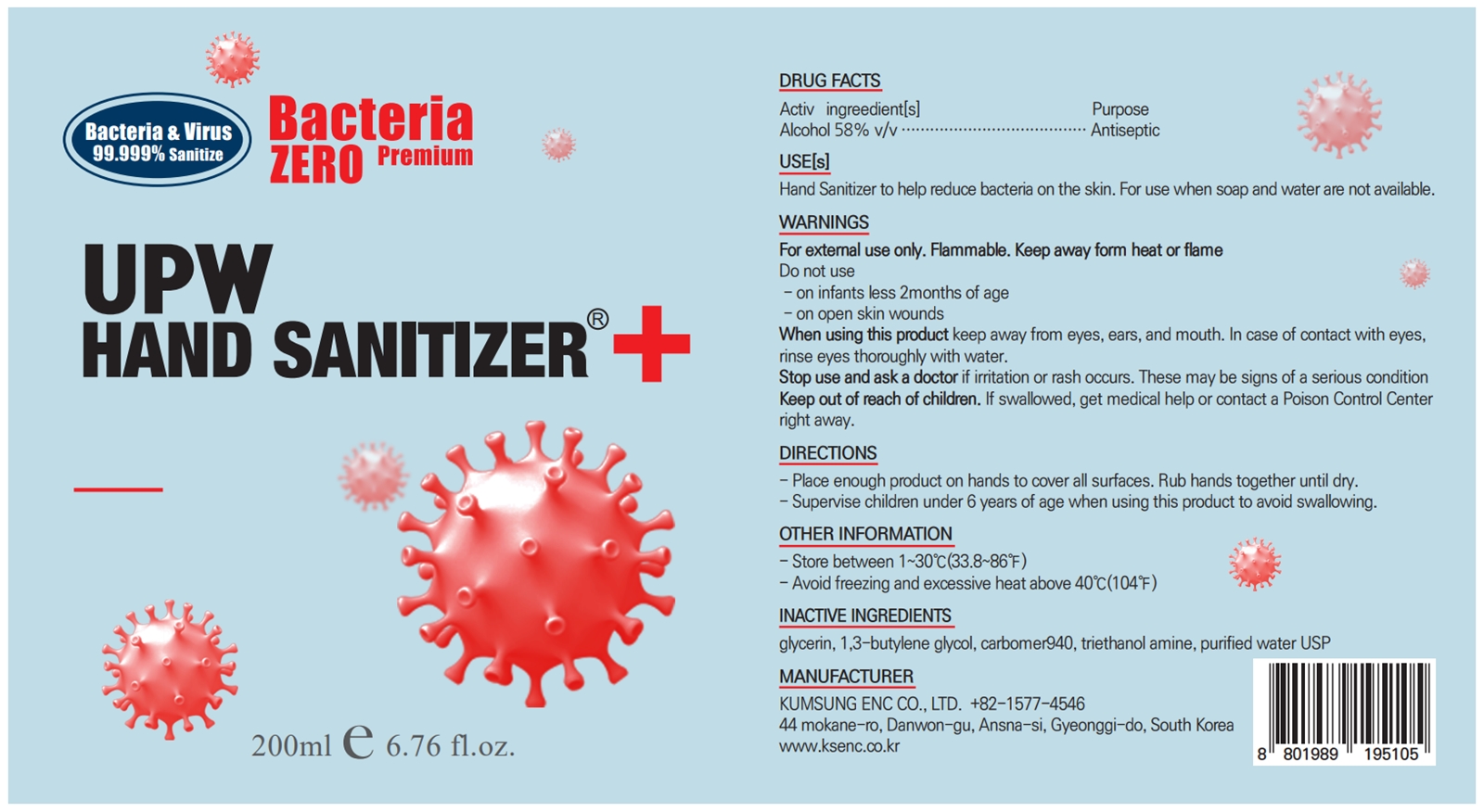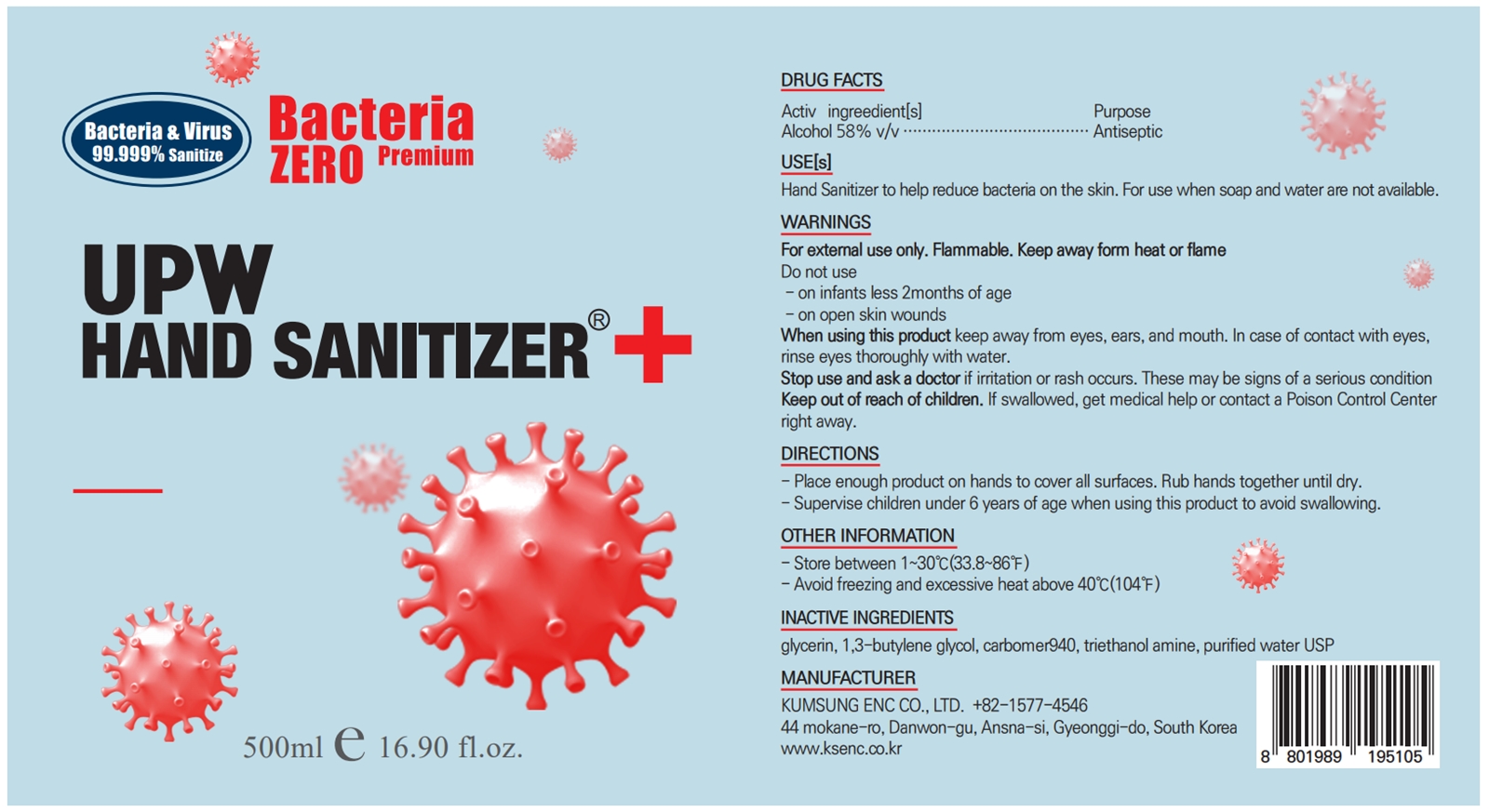 DRUG LABEL: UPW HAND SANITIZER
NDC: 80138-203 | Form: GEL
Manufacturer: KUMSUNG ENC CO., LTD
Category: otc | Type: HUMAN OTC DRUG LABEL
Date: 20200911

ACTIVE INGREDIENTS: ALCOHOL 58 mL/100 mL
INACTIVE INGREDIENTS: BUTYLENE GLYCOL; TROLAMINE; WATER; GLYCERIN; CARBOMER 940

80138-203

ACTIVE INGREDIENT

Alcohol 58%

PURPOSE

Antiseptic

USE

Hand Sanitizer to help reduce bacteria on the skin. For use when soap and water are not available.

WARNINGS

For external use only. Flammable. Keep away form heat or flame

Do not use

- on infants less 2months of age

- on open skin wounds

WHEN USING THIS PRODUCT

keep away from eyes, ears, and mouth. In case of contact with eyes, rinse eyes thoroughly with water.

STOP USE AND ASK A DOCTOR

if irritation or rash occurs. These may be signs of a serious condition

KEEP OUT OF REACH OF CHILDREN.

If swallowed, get medical help or contact a Poison Control Center right away.

DIRECTIONS

- Place enough product on hands to cover all surfaces. Rub hands together until dry.

- Supervise children under 6 years of age when using this product to avoid swallowing.

OTHER INFORMATION

- Store between 1~30℃(33.8~86℉)

- Avoid freezing and excessive heat above 40℃(104℉)

INACTIVE INGREDIENTS

glycerin, 1,3-butylene glycol, carbomer940, triethanol amine, purified water USP